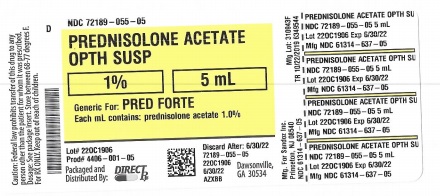 DRUG LABEL: PREDNISOLONE ACETATE
NDC: 72189-055 | Form: SUSPENSION/ DROPS
Manufacturer: DIRECT RX
Category: prescription | Type: HUMAN PRESCRIPTION DRUG LABEL
Date: 20191030

ACTIVE INGREDIENTS: PREDNISOLONE ACETATE 10 mg/1 mL
INACTIVE INGREDIENTS: BENZALKONIUM CHLORIDE; HYPROMELLOSES; SODIUM PHOSPHATE, DIBASIC; POLYSORBATE 80; EDETATE DISODIUM; CITRIC ACID MONOHYDRATE; SODIUM HYDROXIDE; WATER; GLYCERIN

PREDNISOLONE ACETATE

DESCRIPTION

Prednisolone Acetate Ophthalmic Suspension USP, 1% is an adrenocortical steroid product prepared as a sterile ophthalmic suspension. The active ingredient is represented by the chemical structure:

chemical
Established name: Prednisolone Acetate

Chemical name: Pregna-1,4-diene-3,20-dione, 21-(acetyloxy)-11,17-dihydroxy-,(11β)-.

Each mL contains:Active: prednisolone acetate 1.0%. Preservative: benzalkonium chloride 0.01%. Vehicle: hypromellose. Inactives: dibasic sodium phosphate, polysorbate 80, edetate disodium, glycerin, citric acid and/or sodium hydroxide (to adjust pH), purified water.

CLINICAL PHARMACOLOGY

Corticosteroids inhibit the inflammatory response to a variety of inciting agents and probably delay or slow healing. They inhibit the edema, fibrin deposition, capillary dilation, leukocyte migration, capillary proliferation, fibroblast proliferation, deposition of collagen, and scar formation associated with inflammation. There is no generally accepted explanation for the mechanism of action of ocular corticosteroids. However, corticosteroids are thought to act by the induction of phospholipase A2 inhibitory proteins, collectively called lipocortins. It is postulated that these proteins control the biosynthesis of potent mediators of inflammation such as prostaglandins and leukotrienes by inhibiting the release of their common precursor arachidonic acid. Arachidonic acid is released from membrane phospholipids by phospholipase A2.

Corticosteroids are capable of producing a rise in intraocular pressure.

INDICATIONS AND USAGE

Steroid responsive inflammatory conditions of the palpebral and bulbar conjunctiva, cornea, and anterior segment of the globe such as allergic conjunctivitis, acne rosacea, superficial punctate keratitis, herpes zoster keratitis, iritis, cyclitis, selected infective conjunctivitides, when the inherent hazard of steroid use is accepted to obtain an advisable diminution in edema and inflammation; corneal injury from chemical, radiation, or thermal burns, or penetration of foreign bodies.

CONTRAINDICATIONS

Prednisolone Acetate Ophthalmic Suspension USP, 1% is contraindicated in most viral diseases of the cornea and conjunctiva including epithelial herpes simplex keratitis (dendritic keratitis), vaccinia, and varicella, and also in mycobacterial infection of the eye and fungal diseases of ocular structures. Prednisolone Acetate Ophthalmic Suspension USP, 1% is also contraindicated in individuals with known or suspected hypersensitivity to any of the ingredients of this preparation and to other corticosteroids.

WARNINGS

FOR TOPICAL OPHTHALMIC USE ONLY. Prolonged use of corticosteroids may result in glaucoma with damage to the optic nerve, defects in visual acuity and fields of vision, and in posterior subcapsular cataract formation. Prolonged use may also suppress the host immune response and thus increase the hazard of secondary ocular infections. Various ocular diseases and long-term use of topical corticosteroids have been known to cause corneal and scleral thinning. Use of topical corticosteroids in the presence of thin corneal or scleral tissue may lead to perforation. Acute purulent infections of the eye may be masked or activity enhanced by the presence of corticosteroid medication. If this product is used for 10 days or longer, intraocular pressure should be routinely monitored even though it may be difficult in children and uncooperative patients. Steroids should be used with caution in the presence of glaucoma. Intraocular pressure should be checked frequently.

The use of steroids after cataract surgery may delay healing and increase the incidence of bleb formation. Use of ocular steroids may prolong the course and may exacerbate the severity of many viral infections of the eye (including herpes simplex). Employment of a corticosteroid medication in the treatment of patients with a history of herpes simplex requires great caution; frequent slit lamp microscopy is recommended. Corticosteroids are not effective in mustard gas keratitis and Sjogren's keratoconjunctivitis.

PRECAUTIONS

General

The initial prescription and renewal of the medication order should be made by a physician only after examination of the patient with the aid of magnification, such as slit lamp biomicroscopy and, where appropriate, fluorescein staining. If signs and symptoms fail to improve after two days, the patient should be re-evaluated.

As fungal infections of the cornea are particularly prone to develop coincidentally with long-term local corticosteroid applications, fungal invasion should be suspected in any persistent corneal ulceration where a corticosteroid has been used or is in use. Fungal cultures should be taken when appropriate.

If this product is used for 10 days or longer, intraocular pressure should be monitored (SEE WARNINGS).

Information for Patients

If inflammation or pain persists longer than 48 hours or becomes aggravated, the patient should be advised to discontinue use of the medication and consult a physician.

This product is sterile when packaged. To prevent contamination, care should be taken to avoid touching the bottle tip to eyelids or to any other surface. The use of this bottle by more than one person may spread infection. Keep bottle tightly closed when not in use. Keep out of the reach of children.

Carcinogenesis, Mutagenesis, Impairment of Fertility

No studies have been conducted in animals or in humans to evaluate the potential of these effects.

Pregnancy

Teratogenic effects

Pregnancy Category C. Prednisolone has been shown to be teratogenic in mice when given in doses 1-10 times the human dose.

Dexamethasone, hydrocortisone and prednisolone were ocularly applied to both eyes of pregnant mice five times per day on days 10 through 13 of gestation. A significant increase in the incidence of cleft palate was observed in the fetuses of the treated mice. There are no adequate and well controlled studies in pregnant women. Prednisolone Acetate Ophthalmic Suspension USP, 1% should be used during pregnancy only if the potential benefit justifies the potential risk to the fetus.

Nursing Mothers

It is not known whether topical administration of corticosteroids could result in sufficient systemic absorption to produce detectable quantities in human milk. Systemically administered corticosteroids appear in human milk and could suppress growth, interfere with endogenous corticosteroid production, or cause other untoward effects. Because of the potential for serious adverse reactions in nursing infants from prednisolone acetate, a decision should be made whether to discontinue nursing or to discontinue the drug, taking into account the importance of the drug to the mother.

PEDIATRIC USE

Safety and effectiveness in pediatric patients have not been established.

GERIATRIC USE

No overall differences in safety or effectiveness have been observed between elderly and younger patients.

ADVERSE REACTIONS

Adverse reactions include, in decreasing order of frequency, elevation of intraocular pressure (IOP) with possible development of glaucoma and infrequent optic nerve damage, posterior subcapsular cataract formation, and delayed wound healing.

Although systemic effects are extremely uncommon, there have been rare occurrences of systemic hypercorticoidism after use of topical steroids.

Corticosteroid-containing preparations have also been reported to cause acute anterior uveitis and perforation of the globe. Keratitis, conjunctivitis, corneal ulcers, mydriasis, conjunctival hyperemia, loss of accommodation and ptosis have occasionally been reported following local use of corticosteroids.

The development of secondary ocular infection (bacterial, fungal and viral) has occurred. Fungal and viral infections of the cornea are particularly prone to develop coincidentally with long-term applications of steroid. The possibility of fungal invasion should be considered in any persistent corneal ulceration where steroid treatment has been used (SEE WARNINGS).

ADVERSE REACTIONS

Adverse reactions include, in decreasing order of frequency, elevation of intraocular pressure (IOP) with possible development of glaucoma and infrequent optic nerve damage, posterior subcapsular cataract formation, and delayed wound healing.

Although systemic effects are extremely uncommon, there have been rare occurrences of systemic hypercorticoidism after use of topical steroids.

Corticosteroid-containing preparations have also been reported to cause acute anterior uveitis and perforation of the globe. Keratitis, conjunctivitis, corneal ulcers, mydriasis, conjunctival hyperemia, loss of accommodation and ptosis have occasionally been reported following local use of corticosteroids.

The development of secondary ocular infection (bacterial, fungal and viral) has occurred. Fungal and viral infections of the cornea are particularly prone to develop coincidentally with long-term applications of steroid. The possibility of fungal invasion should be considered in any persistent corneal ulceration where steroid treatment has been used (SEE WARNINGS).

DOSAGE AND ADMINISTRATION

SHAKE WELL BEFORE USING. Two drops topically in the eye(s) four times daily. In cases of bacterial infections, concomitant use of anti-infective agents is mandatory. Care should be taken not to discontinue therapy prematurely. If signs and symptoms fail to improve after two days, the patient should be re-evaluated (SEE PRECAUTIONS).

The dosing of Prednisolone Acetate Ophthalmic Suspension USP, 1% may be reduced, but care should be taken not to discontinue therapy prematurely. In chronic conditions, withdrawal of treatment should be carried out by gradually decreasing the frequency of applications.

HOW SUPPLIED

Prednisolone Acetate Ophthalmic Suspension USP, 1% is supplied in a white round low density polyethylene DROP-TAINER* dispenser with a natural low density polyethylene dispensing plug and pink polypropylene cap. Tamper evidence is provided with a shrink band around the closure and neck area of the package.